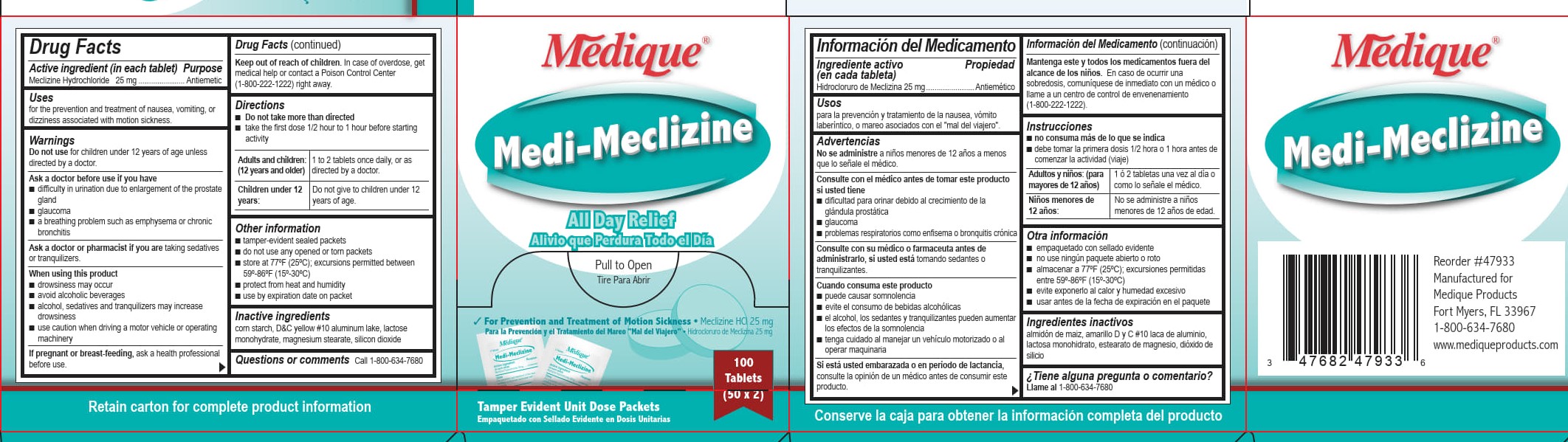 DRUG LABEL: Medique Medi-Meclizine
NDC: 47682-481 | Form: TABLET
Manufacturer: Unifirst First Aid Corporation
Category: otc | Type: HUMAN OTC DRUG LABEL
Date: 20250909

ACTIVE INGREDIENTS: MECLIZINE HYDROCHLORIDE 25 mg/1 1
INACTIVE INGREDIENTS: STARCH, CORN; SILICON DIOXIDE; MAGNESIUM STEARATE; D&C YELLOW NO. 10 ALUMINUM LAKE; LACTOSE MONOHYDRATE

Medique Medi-Meclizine

Active ingredient (in each tablet)

Meclizine Hydrochloride 25 mg

Purpose

Antiemetic

Uses

for the prevention and treatment of the nausea, vomiting, or dizziness associated with motion sickness.

Warnings

Do not use for children under 12 years of age unless directed by a doctor.

Ask a doctor before use if you have

■ difficulty in urination due to enlargement of the prostate gland

■ glaucoma

■ a breathing problems such as emphysema or chronic bronchitis

Ask a doctor or pharmacist before use if you are taking sedatives or tranquilizers.

When using this product

■ drowsiness may occur

■ avoid alcoholic beverages

■ alcohol, sedatives and tranquilizers may increase drowsiness

■ use caution when driving a motor vehicle or operating machinery

PREGNANCY OR BREAST FEEDING

If pregnant or breast-feeding, ask a health professional before use.

Keep out of reach of children. In case of overdose, get medical help or contact a Poison Control Center
(1-800-222-1222) right away.

Directions

- Do not take more than directed
- take the first dose ½ hour to 1 hour before starting activity

Adults and children: (12 years and older) 1 to 2 tablets once daily, or as directed by a doctor.

Children under 12 years: Do not give to children under 12 years of age.

Other information

■ tamper-evident sealed packets

■ do not use any opened or torn packets

■ store at 77°F (25°C); excursions permitted between 59- 86º F (15-30ºC)

■ protect from heat and humidity

■ use by expiration date on packet

Inactive ingredients

corn starch, D&C yellow # 10 aluminum lake, lactose monohydrate, magnesium stearate, silicon dioxide

Questions or comments? Call 1-800-634-7680

Medique Medi-Meclizine Label

Medique®

Medi-Meclizine

All Day Relief

Alivio que Perdura Todo el Dia

Pull to Open

Tire Para Abrir

For the Prevention and Treatment of Motion Sickness • Meclizine HCl 25mg

Para la Prevencion y el Tratamiento del Mareo “Mal del Viajero” • Hidrochloruro de Meclizina 25mg

100 Tablets

(50 x 2)

Tamper Evident Unit Dose Packets

Empaquetado con Sellado Evidente en Dosis Unitarias